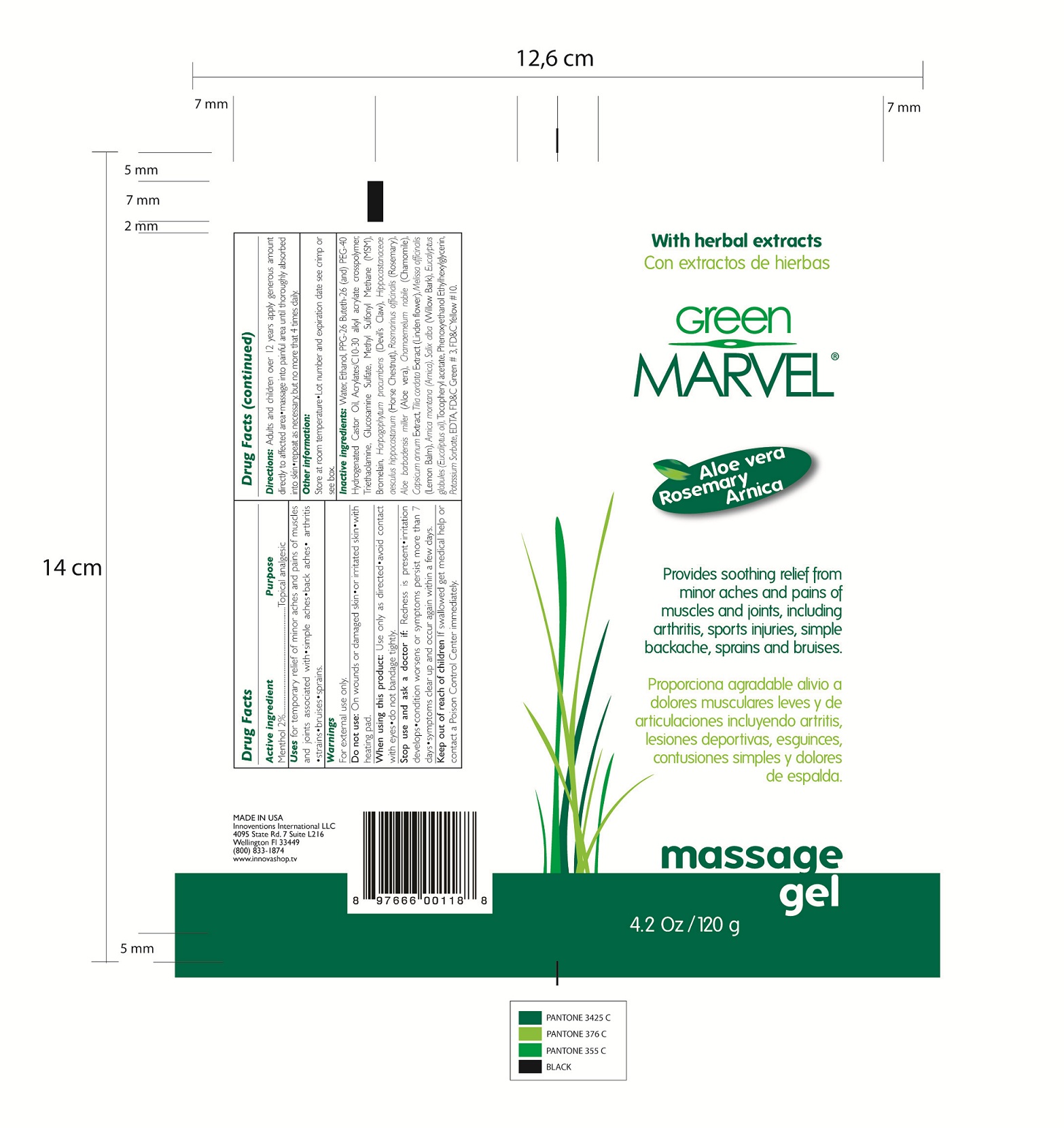 DRUG LABEL: PAIN RELIEVER
NDC: 35192-002 | Form: GEL
Manufacturer: CA-BOTANA INTERNATIONAL
Category: otc | Type: HUMAN OTC DRUG LABEL
Date: 20110824

ACTIVE INGREDIENTS: MENTHOL 2.4 g/120 g
INACTIVE INGREDIENTS: WATER; ETHANOL; HYDROGENATED CASTOR OIL; CARBOMER COPOLYMER TYPE A; TROLAMINE; GLUCOSAMINE SULFATE; DIMETHYL SULFONE; BROMELAINS; HARPAGOPHYTUM PROCUMBENS ROOT; HORSE CHESTNUT; ROSMARINUS OFFICINALIS FLOWER; ALOE FEROX LEAF; CHAMAEMELUM NOBILE; CAPSICUM; TILIA CORDATA FLOWER; MELISSA OFFICINALIS; ARNICA MONTANA; SALIX ALBA LEAF; EUCALYPTUS GLOBULUS LEAF; .ALPHA.-TOCOPHEROL ACETATE, D-; PHENOXYETHANOL; ETHYLHEXYLGLYCERIN; POTASSIUM SORBATE; EDETIC ACID

GREEN MARVEL MASSAGE GEL WITH HERBAL EXTRACTS.

Warnings:
For external use only.
Do not use on wounds or damaged skin
When using this product: use only as directed. Avoid contact with eyes. Do no bandage tightly
Stop use and ask a doctor if: redness is present. Irritation develops. Condition worsens or symptoms persist more than 7 days. Symptoms clear up and occur again within a few days.
Store at room temperature. Lot number and expiration date see crimp or see box.

Directions:
Adults and children over 12 year. Apply generous amount directly to affected area. Massage into painful area until thoroughly absorbed into skin. Repeat as necessary, but no more that 4 times daily.

INACTIVE INGREDIENTS:
Water. Ethanol. PPG-26 Buteth-26 (and) PEG-40. Hydrogenated Castor Oil. Acrylates/C10-30 alkyl acrylate crosspolymer. Triethanolamine. Glucosamine Sulfate. Methyl Sulfonyl Methane. (MSM). Bromelain. Harpagophytum procumbens (Devil's Claw). Hippocastanaceae aesculus hippocastanum (Horse Chestnut). Rosmarinus officinalis. Aloe barbadenis miller. Chamaemelum nobile. Capsicum annuun Extract. Tilia cordata Extract (Linden flower). Melissa officinalis. Arnica montana. Saliz alba. Eucalyptus globoulus. Tocopheryl acetate. Phenoxyethanol Ethylhexyglycerin. Potassium Sorbate. EDTA. FD and C Green # 3. FD and C Yellow # 10

PURPOSE

Uses for temporary relief of minor aches and pains of muscles and joint associated with: simple aches, back aches, arthritis, strains, bruises, sprains.

ACTIVE INGREDIENT

Menthol 2% Topical analgesic

Keep out of reach of children. If swallowed get medical help or contact a Posion Control Center immediately.

INDICATIONS AND USAGE

Enter section text here